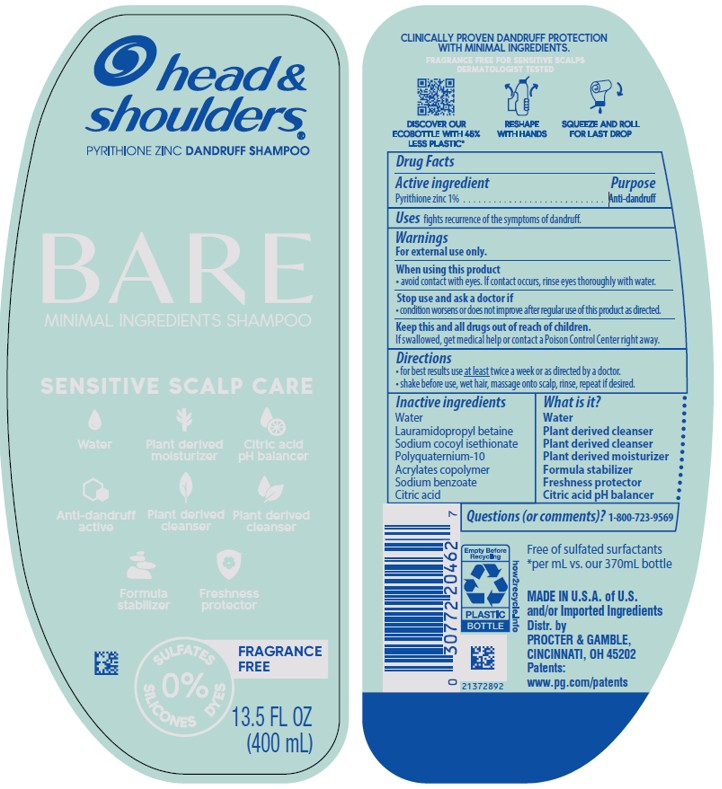 DRUG LABEL: Head and Shoulders Bare Minimal Ingredients Sensitive Scalp Care
NDC: 84126-154 | Form: SHAMPOO
Manufacturer: The Procter & Gamble Manufacturing Company
Category: otc | Type: HUMAN OTC DRUG LABEL
Date: 20260218

ACTIVE INGREDIENTS: PYRITHIONE ZINC 1 g/100 mL
INACTIVE INGREDIENTS: POLYQUATERNIUM-10 (30000 MPA.S AT 2%); SODIUM BENZOATE; CITRIC ACID; SODIUM COCOYL ISETHIONATE; WATER; BUTYL ACRYLATE/METHYL METHACRYLATE/METHACRYLIC ACID COPOLYMER (18000 MW); LAURAMIDOPROPYL BETAINE

Head and Shoulders® Bare Minimal Ingredients Sensitive Scalp Care Shampoo

Drug Facts

Active ingredient

Pyrithione zinc 1%

Purpose

Anti-dandruff

Uses

fights recurrence of the symptoms of dandruff.

Warnings

For external use only.

When using this product

- avoid contact with eyes. If contact occurs, rinse eyes thoroughly with water.

Stop use and ask a doctor if

- condition worsens or does not improve after regular use of this product as directed.

KEEP OUT OF REACH OF CHILDREN

Keep this and all drugs out of reach of children. If swallowed, get medical help or contact a Poison Control Center right away.

Directions

- for best results use at least twice a week or as directed by a doctor.
- shake before use, wet hair, massage onto scalp, rinse, repeat if desired.

Inactive Ingredients

Water, lauramidopropyl betaine, sodium cocoyl isethionate, polyquaternium-10, acrylates copolymer, sodium benzoate, citric acid

Questions (or comments)?

1-800-723-9569

Dist. by PROCTER & GAMBLE,
CINCINNATI, OH 45202

PRINCIPAL DISPLAY PANEL - 400 mL Bottle Label

head &
shoulders®
PYRITHIONE ZINC DANDRUFF SHAMPOO

BARE

MINIMAL INGREDIENTS SHAMPOO

SENSITIVE SCALP CARE

0% SULFATES

DYES

SILICONES

13.5 FL OZ
(400 mL)